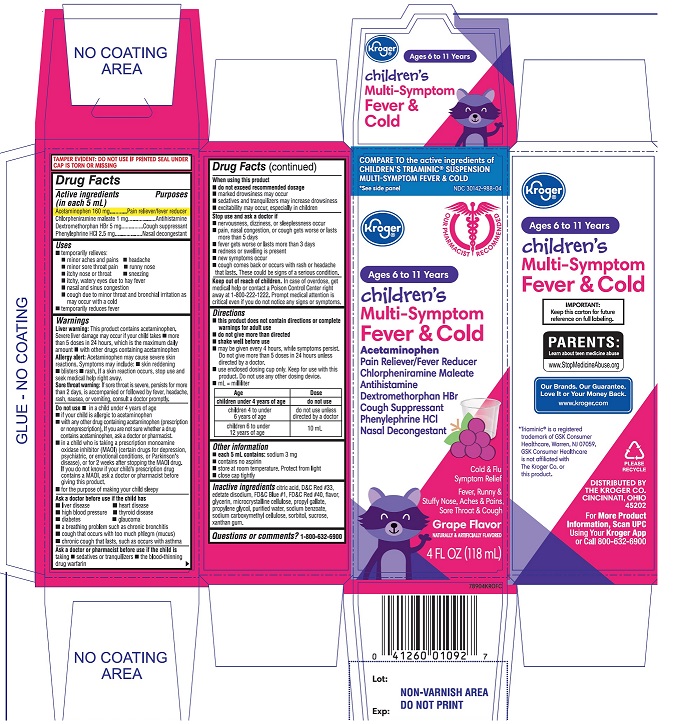 DRUG LABEL: Childrens Multi Symptom Fever and Cold
NDC: 30142-988 | Form: SUSPENSION
Manufacturer: THE KROGER CO.
Category: otc | Type: HUMAN OTC DRUG LABEL
Date: 20250812

ACTIVE INGREDIENTS: ACETAMINOPHEN 160 mg/5 mL; CHLORPHENIRAMINE MALEATE 1 mg/5 mL; DEXTROMETHORPHAN HYDROBROMIDE 5 mg/5 mL; PHENYLEPHRINE HYDROCHLORIDE 2.5 mg/5 mL
INACTIVE INGREDIENTS: ANHYDROUS CITRIC ACID; D&C RED NO. 33; EDETATE DISODIUM; FD&C BLUE NO. 1; FD&C RED NO. 40; GLYCERIN; MICROCRYSTALLINE CELLULOSE; PROPYL GALLATE; PROPYLENE GLYCOL; WATER; SODIUM BENZOATE; CARBOXYMETHYLCELLULOSE SODIUM, UNSPECIFIED; SORBITOL; SUCROSE; XANTHAN GUM

Children’s Multi-Symptom Fever & Cold 4 FL OZ (118 mL) Grape Flavor

Active ingredients (in each 5 mL)

Acetaminophen 160 mg
Chlorpheniramine maleate 1 mg
Dextromethorphan HBr 5 mg
Phenylephrine HCl 2.5 mg

Purposes

Pain reliever/fever reducer
Antihistamine
Cough suppressant
Nasal decongestant

Uses

- temporarily relieves
  - minor aches and pains
  - headache
  - minor sore throat pain
  - runny nose
  - itchy nose or throat
  - sneezing
  - itchy, watery eyes due to hay fever
  - nasal and sinus congestion
  - cough due to minor throat and bronchial irritation as may occur with a cold
- temporarily reduces fever

Warnings

Liver warning:This product contains acetaminophen. Severe liver damage may occur if your child takes

- more than 5 doses in 24 hours, which is the maximum daily amount
- with other drugs containing acetaminophen

Allergy alert:Acetaminophen may cause severe skin reactions. Symptoms may include:

- skin reddening
- blisters
- rash

If a skin reaction occurs, stop use and seek medical help right away.

Sore throat warning:If sore throat is severe, persists for more than 2 days, is accompanied or followed by fever, headache, rash, nausea, or vomiting, consult a doctor promptly.

Do not use

- in a child under 4 years of age
- if your child is allergic to acetaminophen
- with any other drug containing acetaminophen (prescription or nonprescription). If you are not sure whether a drug contains acetaminophen, ask a doctor or pharmacist.
- in a child who is taking a prescription monoamine oxidase inhibitor (MAOI) (certain drugs for depression, psychiatric, or emotional conditions, or Parkinson’s disease), or for 2 weeks after stopping the MAOI drug. If you do not know if your child’s prescription drug contains an MAOI, ask a doctor or pharmacist before taking this product.
- for the purpose of making your child sleepy

Ask a doctor before use if the child has

- liver disease
- heart disease
- high blood pressure
- thyroid disease
- diabetes
- glaucoma
- a breathing problem such as chronic bronchitis
- cough that occurs with too much phlegm (mucus)
- chronic cough that lasts, such as occurs with asthma

Ask a doctor or pharmacist before use if the child is

- taking sedatives or tranquilizers
- taking the blood thinning drug warfarin

When using this product

- do not exceed recommended dosage
- marked drowsiness may occur
- sedatives and tranquilizers may increase drowsiness
- excitability may occur, especially in children

Stop use and ask a doctor if

- nervousness, dizziness, or sleeplessness occur
- pain, nasal congestion or cough gets worse or lasts more than 5 days
- fever gets worse or lasts more than 3 days
- redness or swelling is present
- new symptoms occur
- cough comes back or occurs with rash or headache that lasts. These could be signs of a serious condition.

Keep out of reach of children.

In case of overdose, get medical help or contact a Poison Control Center right away at 1-800-222-1222. Prompt medical attention is critical even if you do not notice any signs or symptoms.

Directions

- this product does not contain directions or complete warnings for adult use
- do not give more than directed
- shake well before use
- may be given every 4 hours, while symptoms persist. Do not give more than 5 doses in 24 hours unless directed by a doctor.
- use enclosed dosing cup only. Keep for use with this product. Do not use any other dosing device.
- mL = milliliter

Age | Dose
children under 4 years | do not use
children 4 to under 6 years of age | do not use unless directed by a doctor
children 6 to under 12 years of age | 10 mL

Other information

- each 5 mL contains: sodium 5 mg
- Tamper–evident: do not use if printed inner seal under cap is torn or missing
- store at room temperature. Protect from light.
- contains no aspirin
- close cap tightly

Inactive ingredients

citric acid, D&C Red #33, edetate disodium, FD&C Blue #1, FD&C Red #40, flavor, glycerin, microcrystalline cellulose, propyl gallate, propylene glycol, purified water, sodium benzoate, sodium carboxymethylcellulose, sorbitol, sucrose, xanthan gum

Questions or comments?

1-866-467-2748

Principal Display Panel

NDC 30142-988-04

Compare to the active ingredients in Children’s Triaminic®Suspension Multi-Symptom Fever & Cold*

Children’s Multi-Symptom

Fever & Cold

ACETAMINOPHEN /

Pain Reliever/Fever Reliever

CHLORPHENIRAMINE MALEATE /

Antihistamine

DEXTROMETHORPHAN HBR /

Cough Suppressant

PHENYLEPHRINE HCL /

Nasal Decongestant

- Cold & Flu Symptoms Relief
- Fever
- Runny & Stuffy Nose
- Aches & Pains
- Sore Throat
- Cough

Grape Flavor

Ages 6-11 Years

Naturally and artificially flavored

4 FL OZ (118 mL)

IMPORTANT: Keep this carton for future reference on full labeling

*This product is not manufactured or distributed by GSK Consumer Healthcare, owner of the registered trademark Children’s Triaminic Suspension Multi-Symptom Fever & Cold.

Distributed by: